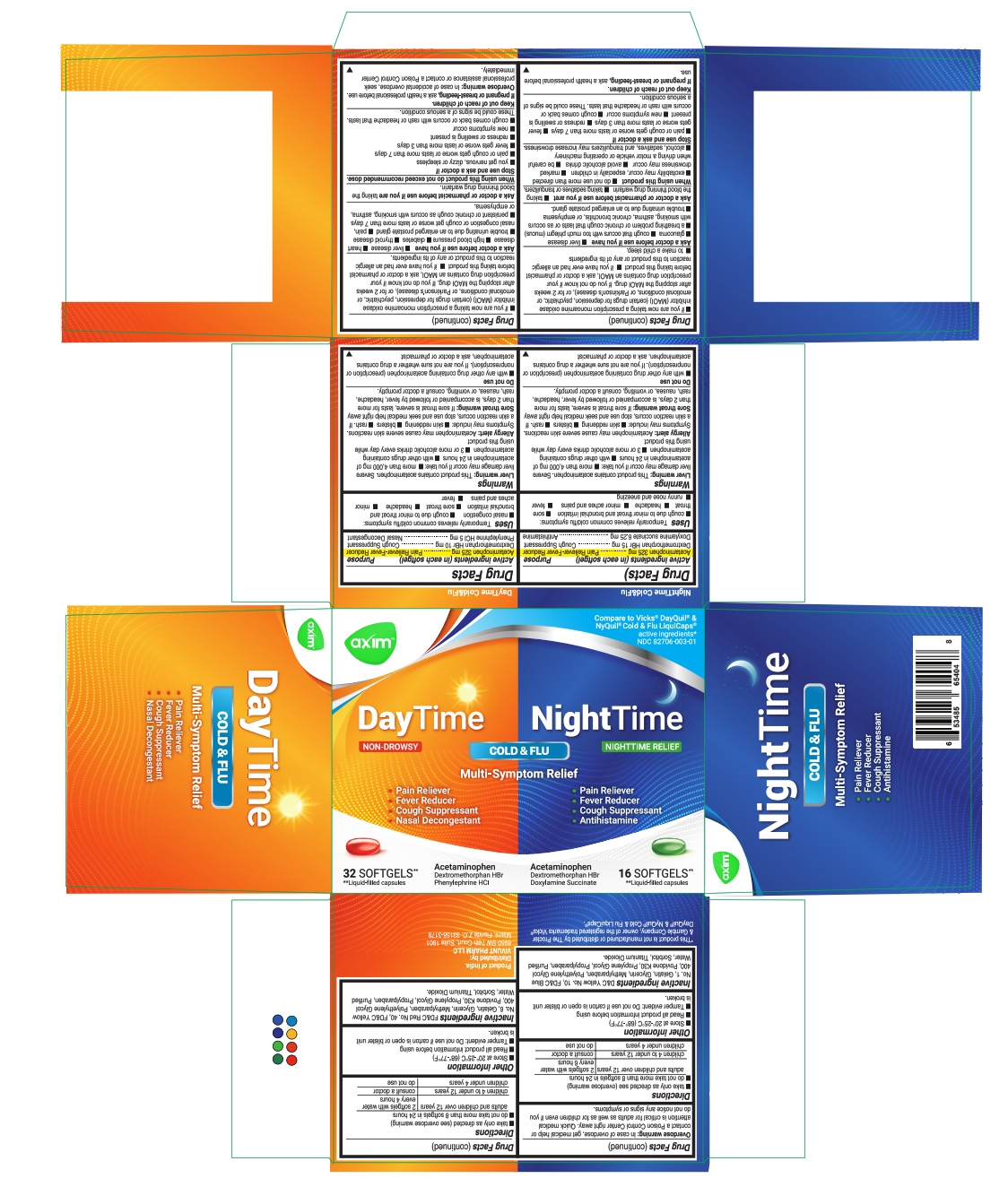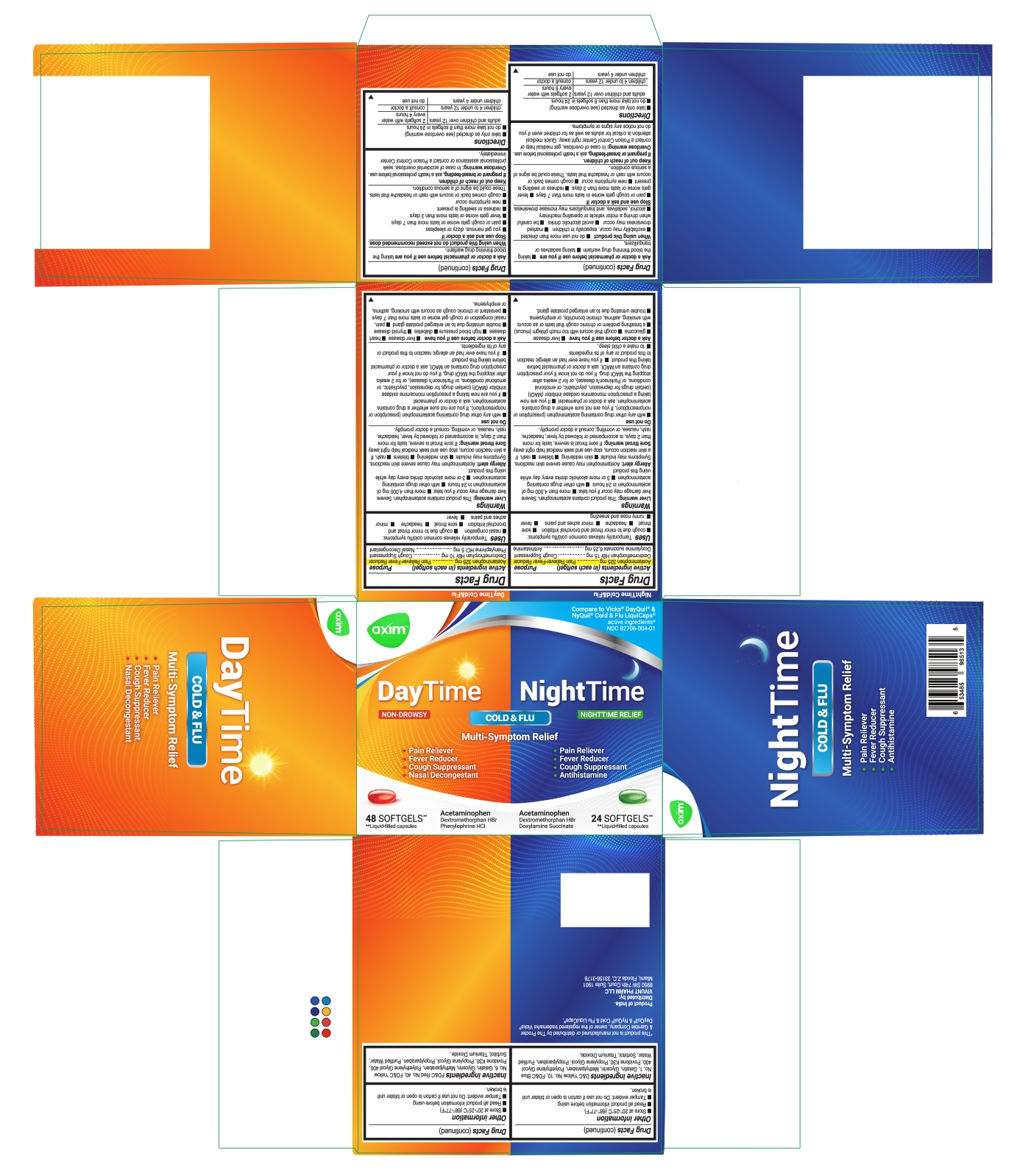 DRUG LABEL: AXIM DayTime - Night Time 48 Softgels
NDC: 82706-003 | Form: KIT | Route: ORAL
Manufacturer: VIVUNT PHARMA LLC
Category: otc | Type: HUMAN OTC DRUG LABEL
Date: 20251029

ACTIVE INGREDIENTS: DEXTROMETHORPHAN HYDROBROMIDE 10 mg/1 1; ACETAMINOPHEN 325 mg/1 1; PHENYLEPHRINE HYDROCHLORIDE 5 mg/1 1; DEXTROMETHORPHAN HYDROBROMIDE 15 mg/1 1; ACETAMINOPHEN 325 mg/1 1; DOXYLAMINE SUCCINATE 6.25 mg/1 1
INACTIVE INGREDIENTS: PROPYLPARABEN; METHYLPARABEN; WATER; GELATIN; GLYCERIN; TITANIUM DIOXIDE; POVIDONE K30; POLYETHYLENE GLYCOL 400; PROPYLENE GLYCOL; FD&C YELLOW NO. 6; FD&C RED NO. 40; SORBITOL; PROPYLPARABEN; METHYLPARABEN; POLYETHYLENE GLYCOL 400; PROPYLENE GLYCOL; GELATIN; FD&C BLUE NO. 1; POVIDONE K30; WATER; TITANIUM DIOXIDE; GLYCERIN; D&C YELLOW NO. 10; SORBITOL

AXIM DayTime & Night Time

Day Time

Drug Facts

ACTIVE INGREDIENT

Active ingredients (in each softgel) | Purpose
Acetaminophen 325 mg | Pain Reliever-fever reducer
Dextrometrophan HBr 10 mg | Cough Suppressant
Phenylephrine HCl 5 mg | Nasal Decongestant

Uses

Temporarily relieves common cold/flu symptoms:

- nasal congestion
- cough due to minor throat and bronchial irritation
- sore throat
- headache
- minor aches and pains
- fever

Warnings

Liver warning

This product contains acetaminophen. Severe liver damage may occur if you take

- more than 4,000 mg of acetaminophen in 24 hours
- with other drugs containing acetaminophen
- 3 or more alcoholic drinks every day while using this product

Allergy Alert

Allergy alert: Acetaminophen may cause severe skin reactions. Symptoms may include:

- skin reddening
- blisters
- rash

If a skin reaction occurs, stop use and seek medical help right away.

Sore throat warning: If sore throat is severe, lasts for more than 2 days, is accompanied or followed by fever, headache, rash, nausea, or vomiting, consult a doctor promptly.

Do not use

- with any other drug containing acetaminophen (prescription or nonprescription). If you are not sure whether a drug contains acetaminophen, ask a doctor or pharmacist.
- if you are now taking a prescription monoamine oxidase inhibitor (MAOI) (certain drugs for depression, psychiatric, or emotional conditions, or Parkinson's disease), or for 2 weeks after stopping the MAOI drug. If you do not know if your prescription drug contains an MAOI, ask a doctor or pharmacist before taking this product.
- if you have ever had an allergic reaction to this product or any of its ingredients

Ask a doctor before use if you have

- liver disease
- heart disease
- high blood pressure
- diabetes
- thyroid disease
- trouble urinating due to an enlarged prostate gland
- cough that occurs with too much phlegm (mucus)
- persistent or chronic cough as occurs with smoking, asthma, or emphysema

Ask a doctor or pharmacist before use if you are

taking the blood thinning drug warfarin.

When using this product

do not exceed recommended dose

Stop use and ask a doctor if

- you get nervous, dizzy or sleepless
- pain or cough gets worse or lasts more than 7 days
- fever gets worse or lasts more than 3 days
- redness or swelling is present
- new symptoms occur
- cough comes back or occurs with rash or headache that lasts.

These could be signs of a serious condition

Keep out of reach of children.

If pregnant or breast-feeding

ask a health professional before use.

Overdose warning

In case of accidental overdose, seek professional assistance or contact a poison control center immediately.

Directions

- Take only as directed (see overdose warning):
- Do not take more than 8 softgels in 24 hours.

adults and children over 12 years | 2 softgels with water every 4 hours
children 4 to under 12 years | consult a doctor
children under 4 years | do not use

Other information

- Store at 20° - 25 °C (68 °- 77 °F)
- Read all product information before using
- Tamper evident: Do not use if carton is open or blister unit is broken.

Inactive ingredients

FD&C Red No. 40, FD&C Yellow No. 6, Gelatin, Glycerin, Methylparaben, Polyethylene Glycol 400, Povidone K30, Propylene Glycol, Propylparaben, Purified Water, Sorbitol, Titanium Dioxide

Night Time

Drug Facts

ACTIVE INGREDIENT

Active ingredients (in each softgel) | Purpose
Acetaminophen 325 mg | Pain reliever/fever reducer
Dextromethorphan HBr 15 mg | Cough suppressant
Doxylamine succinate 6.25 mg | Antihistamine

Uses

Temporarily relieves common cold/flu symptoms:

- cough due to minor throat & bronchial irritation
- sore throat
- headache
- minor aches & pains
- fever
- runny nose & sneezing

Warnings

Liver warning

This product contains acetaminophen. Severe liver damage may occur if you take

- more than 4000 mg of acetaminophen in 24 hours.
- with other drugs containing acetaminophen
- 3 or more alcoholic drinks every day while using this product

Allergy Alert

Allergy alert: Acetaminophen may cause severe skin reactions. Symptoms may include:

- skin reddening
- blisters
- rash

If a skin reaction occurs, stop use and seek medical help right away.

Sore throat warning

If sore throat is severe, lasts for more than 2 days, is accompanied or followed by fever, headache, rash, nausea, or vomiting, consult a doctor promptly.

Do not use

- with any other drug containing acetaminophen (prescription or nonprescription). If you are not sure whether a drug contains acetaminophen, ask a doctor or pharmacist.
- if you are now taking a prescription monoamine oxidase inhibitor (MAOI) (certain drugs for depression, psychiatric, or emotional conditions, or Parkinson's disease), or for 2 weeks after stopping the MAOI drug. If you do not know if your prescription drug contains an MAOI, ask a doctor or pharmacist before taking this product.
- if you have ever had an allergic reaction to this product or any of its ingredients
- to make a child sleep

Ask a doctor before use if you have

- liver disease
- glaucoma
- cough that occurs with too much phlegm (mucus)
- a breathing problem or chronic cough that lasts or as occurs with smoking, asthma, chronic bronchitis, or emphysema
- trouble urinating due to enlarged prostate gland

Ask a doctor or pharmacist before use if you are

- taking the blood thinning drug warfarin
- taking sedatives or tranquilizers

When using this product

- do not use more than directed
- excitability may occur, especially in children
- marked drowsiness may occur
- avoid alcoholic drinks
- be careful when driving a motor vehicle or operating machinery
- alcohol, sedatives, and tranquilizers may increase drowsiness

Stop use and ask a doctor if

- pain or cough gets worse or lasts more than 7 days
- fever gets worse or lasts more than 3 days
- redness or swelling is present
- new symptoms occur
- cough comes back or occurs with rash or headache that lasts. These could be signs of a serious condition.

These could be signs of a serious condition.

Keep out of reach of children.

If pregnant or breast-feeding

ask a health professional before use.

Overdose warning

Center right away. Quick medical attention is critical for adults as well as for children even if you do not notice any signs or symptoms

Directions

- Take only as directed (see overdose warning):
- Do not take more than 8 softgels in 24 hours.

adults and children over 12 years | 2 softgels with water every 6 hours
children 4 to under 12 years | consult a doctor
children under 4 years | do not use

Other information

- Store at 20° - 25 °C (68 °- 77 °F)
- Read all product information before using
- Tamper evident: Do not use if carton is open or blister unit is broken.

Inactive ingredients

D&C Yellow No. 10, FD&C Blue No. 1, Gelatin, Glycerin, Methylparaben, Polyethylene Glycol 400, Povidone K30, Propylene Glycol, Propylparaben, Purified Water, Sorbitol, Titanium Dioxide

Product of India

Distributed by:

VIVUNT PHARMA LLC
8950 SW 74th. Court. Suite 1901

Miami, Florida. Z,C. 33156-3178

PRINCIPAL DISPLAY PANEL - 48 Caps Day&Night

Compare to Vicks® DayQuil ® & NyQuil ®

Cold&Flu LiquiCaps®

active ingredients*
NDC 82706-003-01
Day Time

- Pain Reliever
- Fever Reducer
- Cough Suppressant
- Nasal Decongestant

Acetaminophen, Dextromethorphan HBr, Phenylephrine HCl

32 SOFTGELS** **Liquid-filled capsules

Night Time

- Pain Reliever
- Fever Reducer
- Cough Suppressant
- Antihistamine

Acetaminophen, Dextromethorphan HBr, Doxylamine Succinate

16 SOFTGELS** **Liquid-filled capsules

*This product is not manufactured or distributed by The Procter & Gamble

Company, owner of the registered trademarks Vicks® DayQuil ® & NyQuil ®

Cold&Flu LiquiCaps®.

PRINCIPAL DISPLAY PANEL - 72 Caps Day&Night

Compare to Vicks® DayQuil ® & NyQuil ®

Cold&Flu LiquiCaps®

active ingredients*

NDC 82706-004-01

Day Time

- Pain Reliever
- Fever Reducer
- Cough Suppressant
- Nasal Decongestant

Acetaminophen, Dextromethorphan HBr, Phenylephrine HCl

48 SOFTGELS** **Liquid-filled capsules

Night Time

- Pain Reliever
- Fever Reducer
- Cough Suppressant
- Antihistamine

Acetaminophen, Dextromethorphan HBr, Doxylamine Succinate

24 SOFTGELS** **Liquid-filled capsules

*This product is not manufactured or distributed by The Procter & Gamble

Company, owner of the registered trademarks Vicks® DayQuil ® & NyQuil ®

Cold&Flu LiquiCaps®.